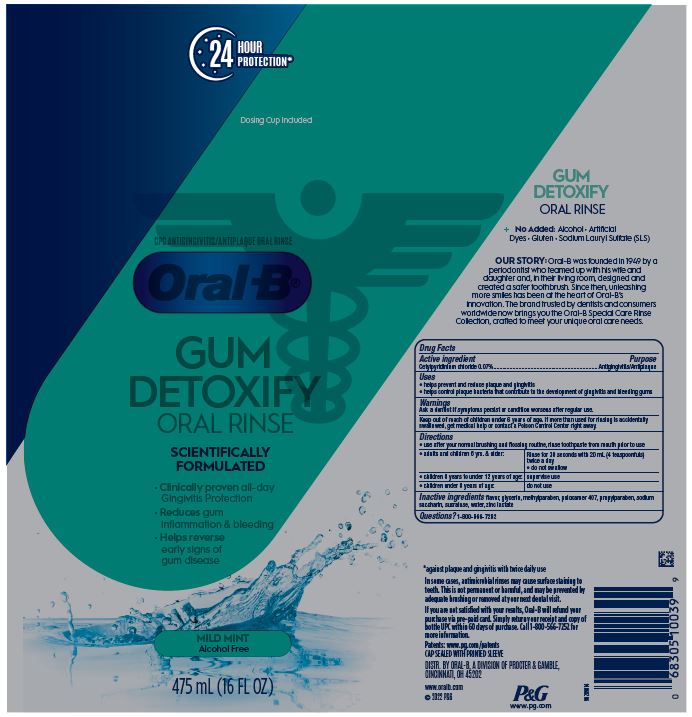 DRUG LABEL: Oral B Gum Detoxify
NDC: 69423-906 | Form: RINSE
Manufacturer: The Procter & Gamble Manufacturing Company
Category: otc | Type: HUMAN OTC DRUG LABEL
Date: 20250806

ACTIVE INGREDIENTS: CETYLPYRIDINIUM CHLORIDE 0.07 g/1 mL
INACTIVE INGREDIENTS: WATER; GLYCERIN; SACCHARIN SODIUM; METHYLPARABEN; PROPYLPARABEN; POLOXAMER 407; SUCRALOSE; ZINC LACTATE

Oral-B Gum Detoxify Special Care Rinse

Drug Facts

Active ingredient

Cetylpyridinium chloride 0.07%

Purpose

Antigingivitis/Antiplaque

Uses

- helps prevent and reduce plaque and gingivitis
- helps control plaque bacteria that contribute to the development of gingivitis and bleeding gums

Warning

WARNINGS

Ask a dentist if symptoms persist or condition worsens after regular use.

Keep out of reach of children 6 years of age. If more than used for rinsing is accidentally swallowed, get medical help or contact a Poison Control Center right away.

Directions

- use after your normal brushing and flossing routine, rinse toothpaste from mouth prior to use
- adults and children 6 yrs. & older: Rinse for 30 seconds with 20 mL (4 teaspoonfuls) twice a day
- do not swallow
- children 6 years to under 12 years of age: supervise use
- children under 6 years of age: do not use

Inactive ingredients

flavor, glycerin, methylparaben, poloxamer 407, propylparaben, sodium saccharin, sucralose, water, zinc lactate

Questions?

1-800-566-7252

DISTR. BY ORAL-B, A DIVISION

OF PROCTER & GAMBLE,

CINCINNATI, OH 45202

PRINCIPAL DISPLAY PANEL - 475 mL Bottle Label

24 HOUR PROTECTION

Dosing cup included

CPC ANTIGINGIVITIS/ANTIPLAQUE ORAL RINSE

Oral-B

GUM DETOXIFY

SCIENTIFICALLY

FORMULATED

- Clinically proven all-day Gingivitis Protection
- Reduces gum inflammation & bleeding
- Helps reduce early signs of gum disease

MILD MINT

ALCOHOL FREE

475 mL (16 FL OZ)